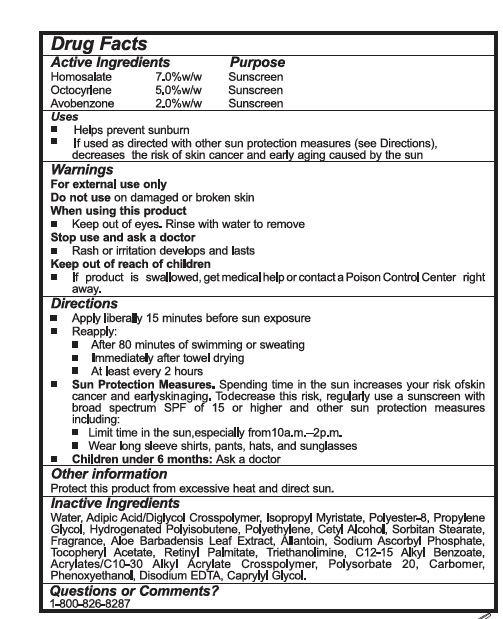 DRUG LABEL: SPF 30 Moisturizer with Aloe Vera
NDC: 83695-001 | Form: CREAM
Manufacturer: Audrey Morris Cosmetics International, LLC
Category: otc | Type: HUMAN OTC DRUG LABEL
Date: 20250731

ACTIVE INGREDIENTS: HOMOSALATE 7 g/100 mL; OCTOCRYLENE 5 g/100 mL; AVOBENZONE 2 g/100 mL
INACTIVE INGREDIENTS: WATER; ADIPIC ACID; ADIPIC ACID/DIGLYCOL CROSSPOLYMER (20000 MPA.S); ISOPROPYL MYRISTATE; POLYESTER-8 (1400 MW, CYANODIPHENYLPROPENOYL CAPPED); PROPYLENE GLYCOL; HYDROGENATED POLYBUTENE (1300 MW); CETYL ALCOHOL; SORBITAN MONOSTEARATE; ALOE VERA LEAF; ALLANTOIN; SODIUM ASCORBYL PHOSPHATE; .ALPHA.-TOCOPHEROL ACETATE; VITAMIN A PALMITATE; TROLAMINE; ALKYL (C12-15) BENZOATE; CARBOMER COPOLYMER TYPE B (ALLYL PENTAERYTHRITOL CROSSLINKED); POLYSORBATE 20; CARBOMER HOMOPOLYMER, UNSPECIFIED TYPE; PHENOXYETHANOL; EDETATE DISODIUM ANHYDROUS; CAPRYLYL GLYCOL

Active Ingredients Purpose

Homosalate 7.0% Sunscreen
Octocrylene 5.0% Sunscreen
Avobenzone 2.0% Sunscreen

Uses

- Helps prevent sunburn
- If used as directed with other sun protection measures (See Directions), decreases the risk of skin cancer and early aging caused by the sun.

Warnings

For Extranal use only
Do not use ondamaged or broken skin.
When using this product

- Keep out of eyes. Rinse with water to remove

Stop use and ask doctor

- Rash or irritation develops and lasts

Keep out of reach if children

- If product gets swallowed, get medical help or contact a Poison Control Center right away

Directions

- Apply liberally 15 minutes before sun exposure
- Reapply:
- After 80 minutes of swimming or sweating
- Immediately after towel drying.
- At least every 2 hours
- Sun Protection Measures: Spending time in the sun increases your risk of skin cancer and early skin aging. To decrease this risk, regularly use a sunscreen with broad spectrum SPF of 15 or higher and other sun protection measures including:
- Limit time in the sun, especially from 10:00a.m – 2:00p.m
- Wear long sleave shirts, pants, hats, and sunglasses.
- Children under 6 Months: Ask a doctor

Other information

Protect this product from excessive heat and direact sun

Inactive Ingredients

Water (Aqua), Adipic Acid, Adipic Acid/Diglycol Crosspolymer, Isopropyl Myristate, Polyester-8, Propylene Glycol, Hydrogenated Polyisobutene, Cetyl alcohol, Sorbitan Stearate, Fragrance, Aloe Barbadensis Leaf Extract, Allantoin, Sodium Ascorbyl Phosphate, Tocopheryl Acetate, Retinyl Palmitate, Triethanolamine, C12-15 Alkyl Benzoate, Acrylates/C10-30 Alkyl Acrylate Crosspolymer, Polysorbate 20, Carbomer, Phenoxyethanol, Disodium EDTA, Caprylyl Glycol.

Questions or Comments?

1-800-826-8287